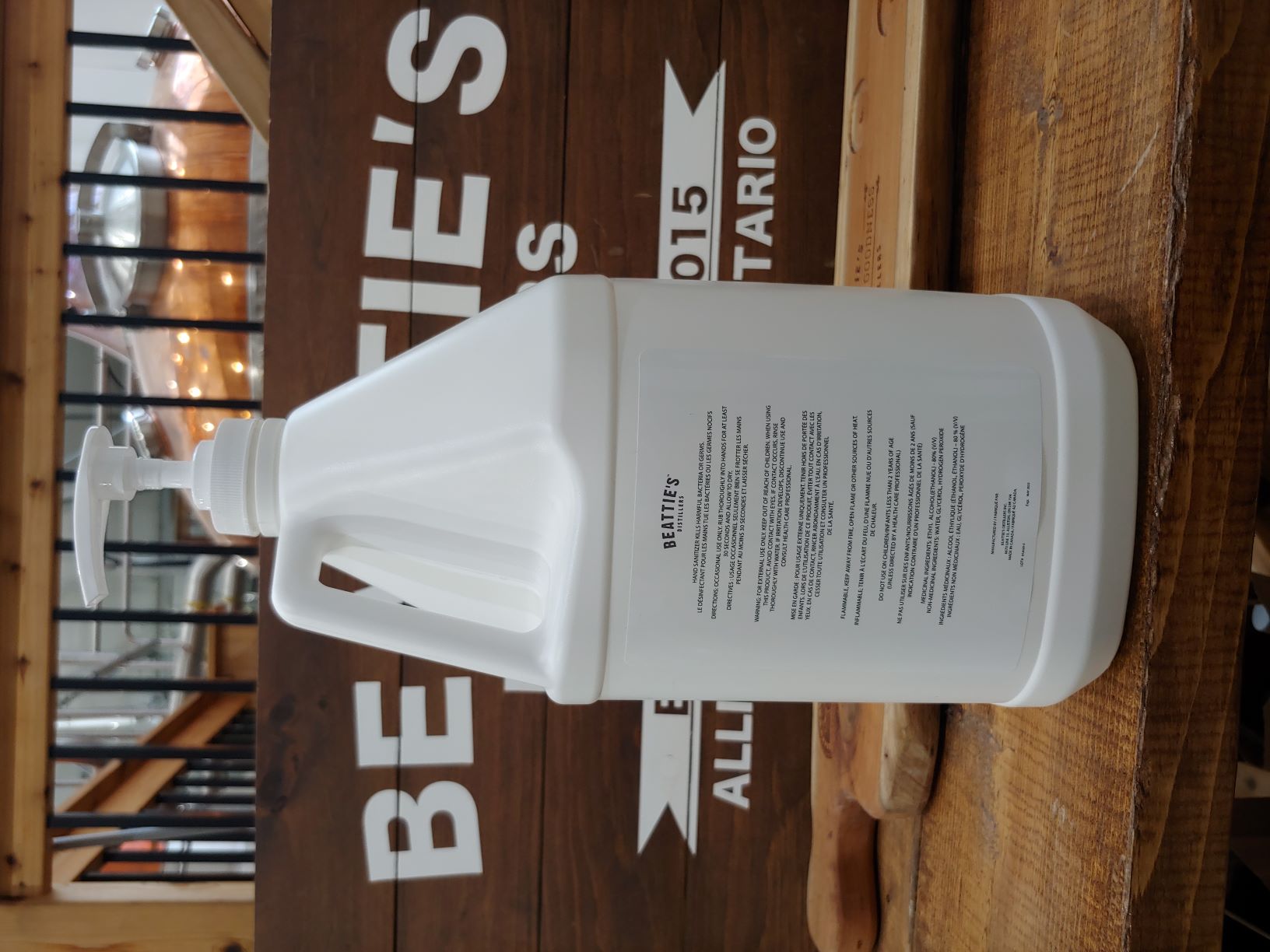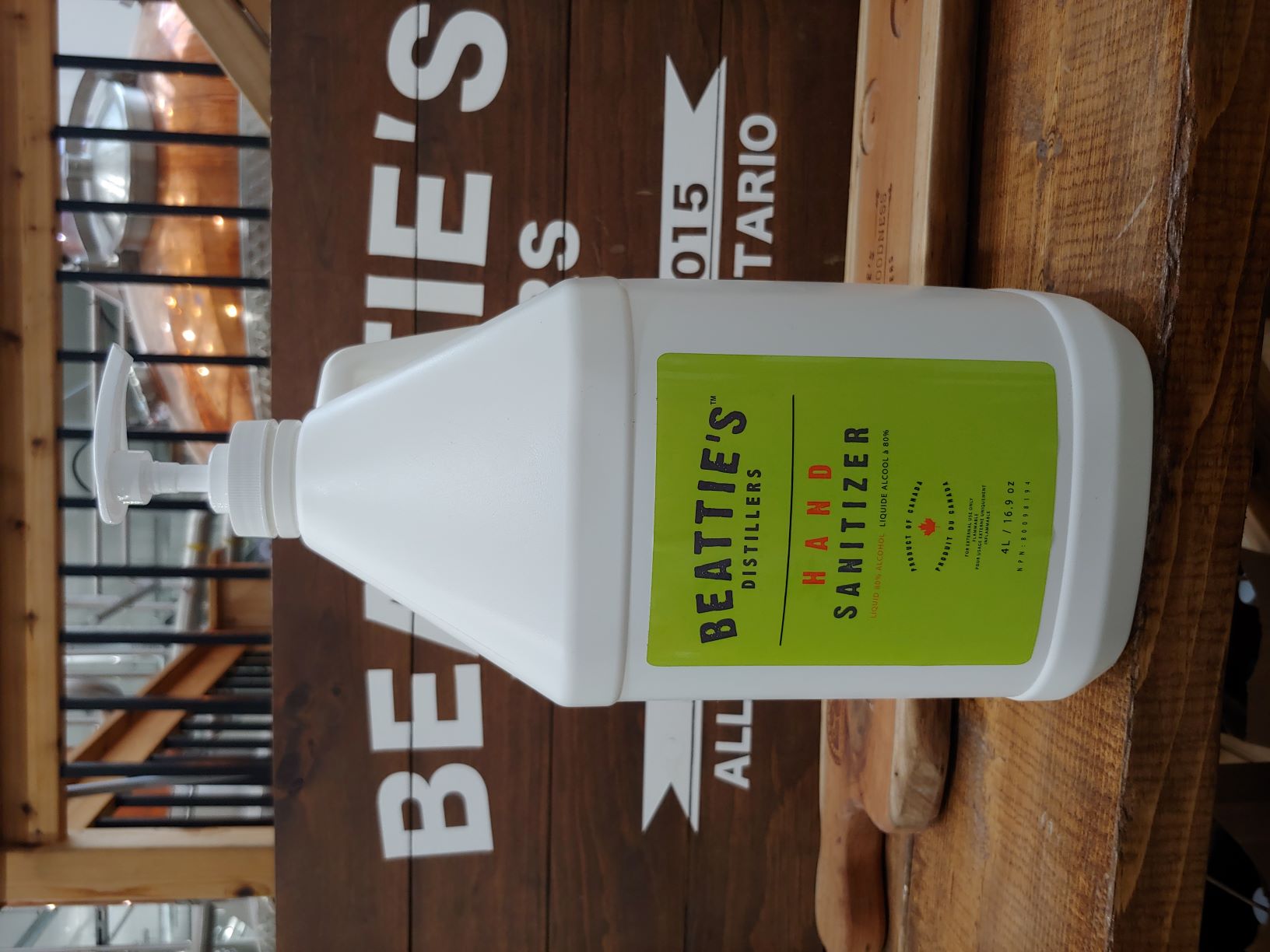 DRUG LABEL: Hand Sanitizer
NDC: 77427-7444 | Form: LIQUID
Manufacturer: Beattie's Distillers Inc.
Category: otc | Type: HUMAN OTC DRUG LABEL
Date: 20220124

ACTIVE INGREDIENTS: ALCOHOL 0.8 L/1 L
INACTIVE INGREDIENTS: GLYCERIN 0.0145 L/1 L; HYDROGEN PEROXIDE 0.00125 L/1 L; WATER

This is a hand sanitizer manufactured according to the Temporary Policy for Preparation of Certain Alcohol-Based Hand Sanitizer Products During the Public Health Emergency (CoViD-19); Guidance for Industry.

The hand sanitizer is manufactured using only the following United States Pharmacopoeia (USP) grade ingredients in the preparation of the product (percentage in final product formulation) consistent with World Health Organization (WHO) recommendations:

1. Alcohol (ethanol) (USP or Food Chemical Codex (FCC) grade) (80%, volume/volume (v/v)) in an aqueous solution denatured according to Alcohol and Tobacco Tax and Trade Bureau regulations in 27 CFR part 20.
2. Glycerol (1.45% v/v).
3. Hydrogen peroxide (0.125% v/v).
4. Sterile distilled water or boiled cold water.

The firm does not add other active or inactive ingredients. Different or additional ingredients may impact the quality and potency of the product.

Active Ingredient(s)

Alcohol 80% v/v. Purpose: Antiseptic

Purpose

Antiseptic, Hand Sanitizer

Use

Hand Sanitizer kills harmful bacteria or germs.

Warnings

Flammable, keep away from fire, open flame or other sources of heat.

Do not use

- in children less than 2 years of age

WHEN USING

For external use only. Keep out of reach of children. When using this product, avoid contact with eyes. If contact occurs, rinse thoroughly with water. If irritation develops, discontinue use and consult health care professional.

Stop use and ask a doctor if irritation or rash occurs.

Keep out of reach of children.

Directions

- Occassional use only. Rub thoroughly into hands for at least 30 seconds and allow to dry.

Other information

- Store between 15-30C (59-86F)
- Avoid freezing and excessive heat above 40C (104F)

Inactive ingredients

glycerin, hydrogen peroxide, purified water USP

Package Label - Principal Display Panel

4 L NDC: 77427-7427-4